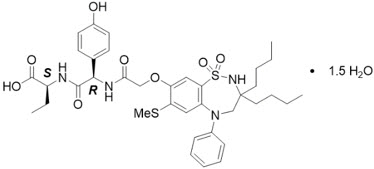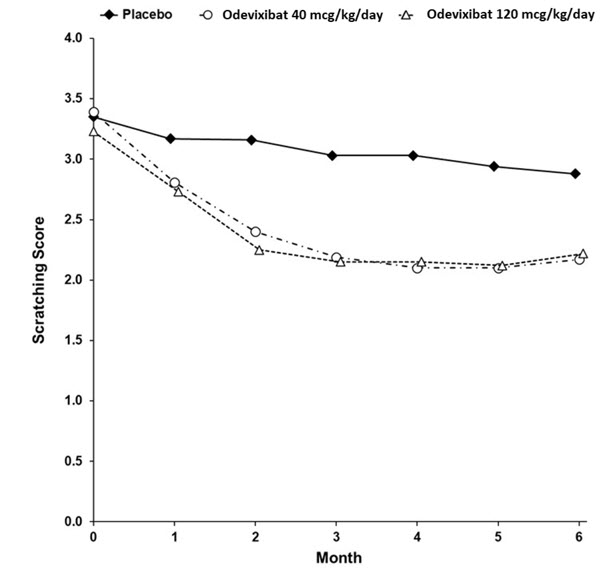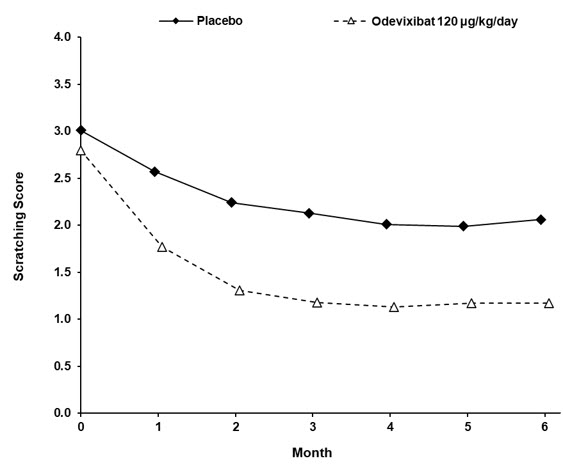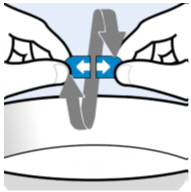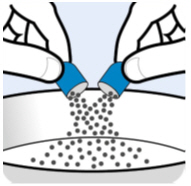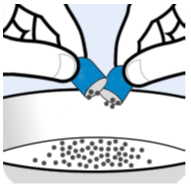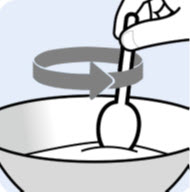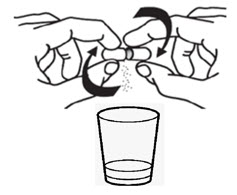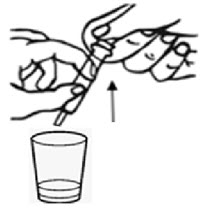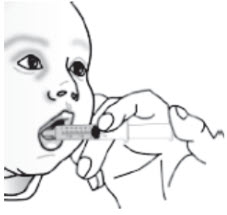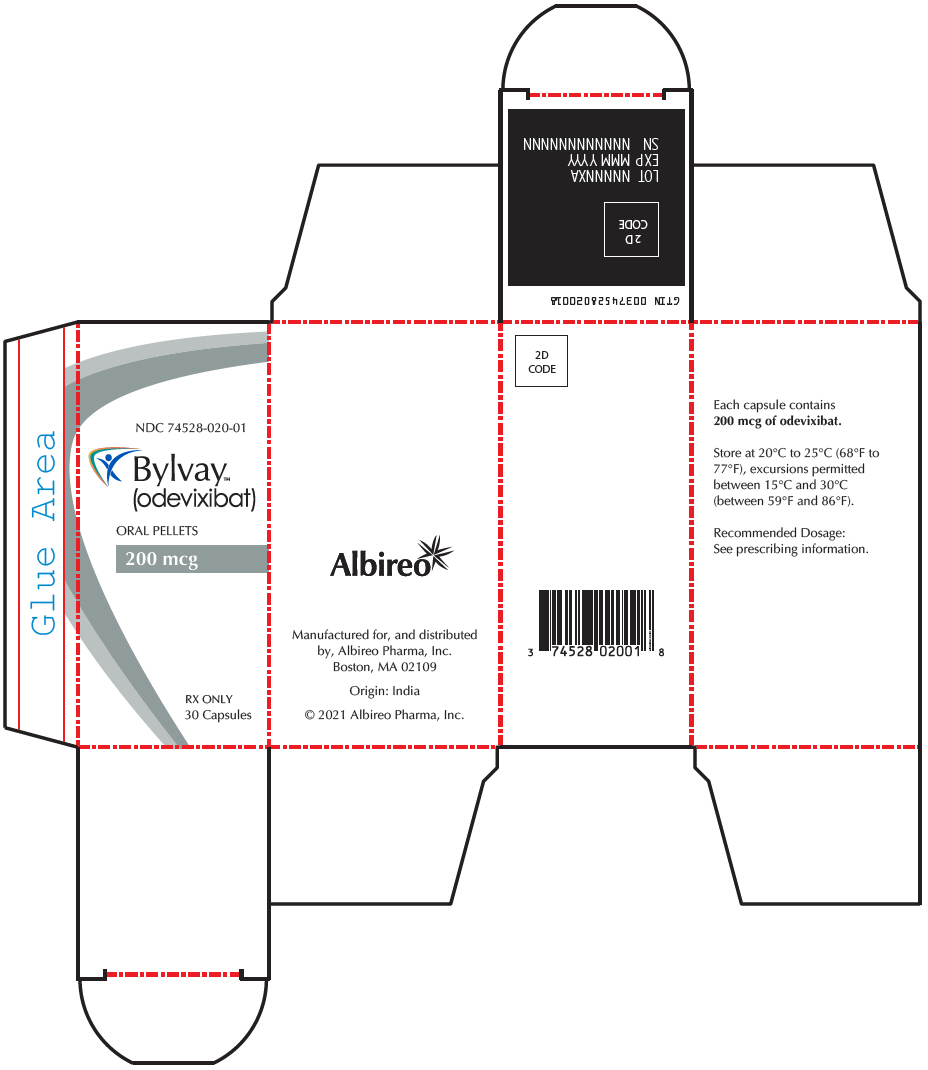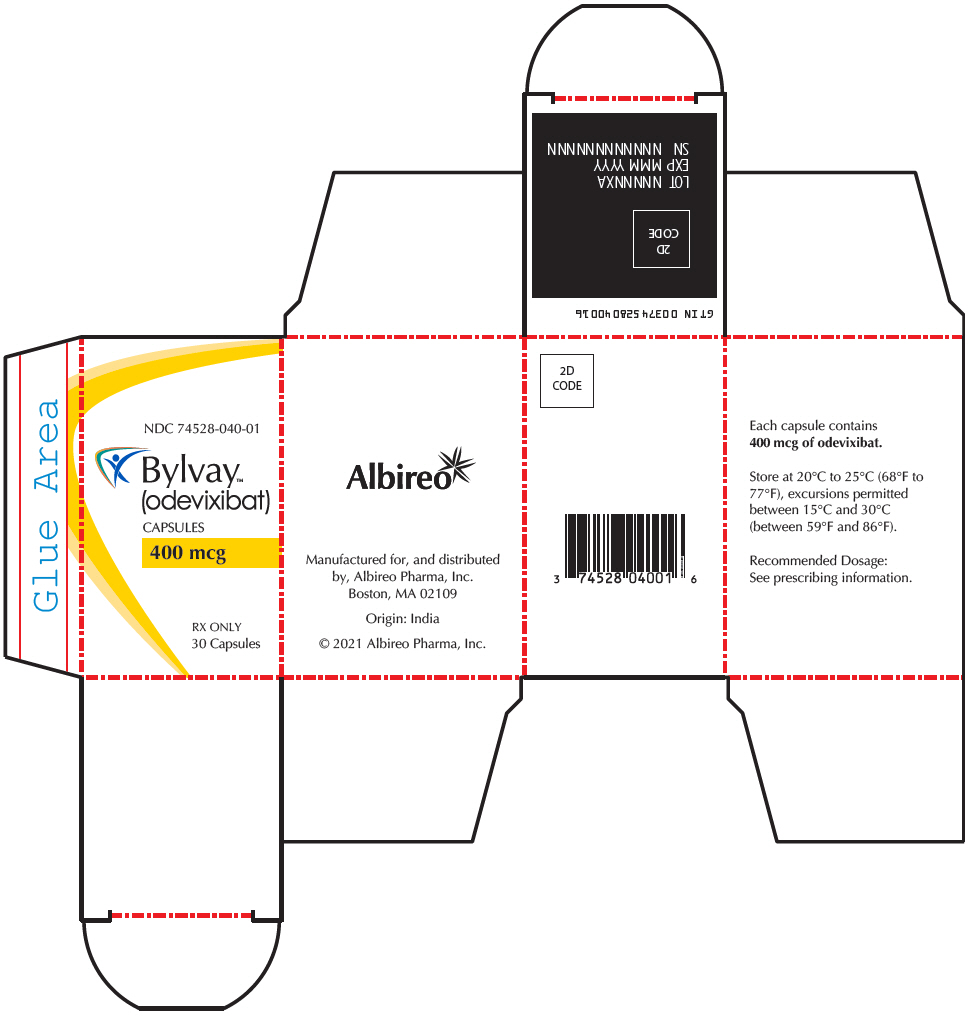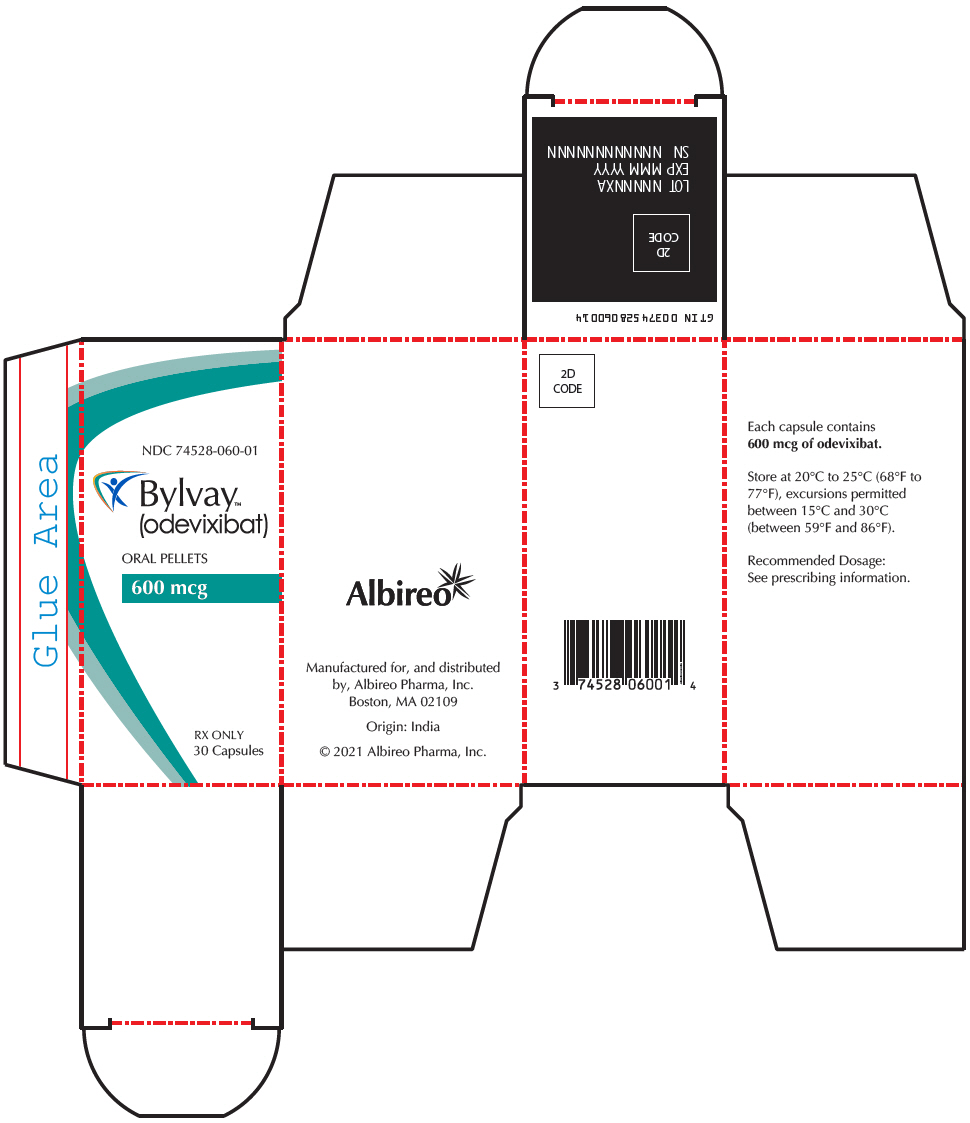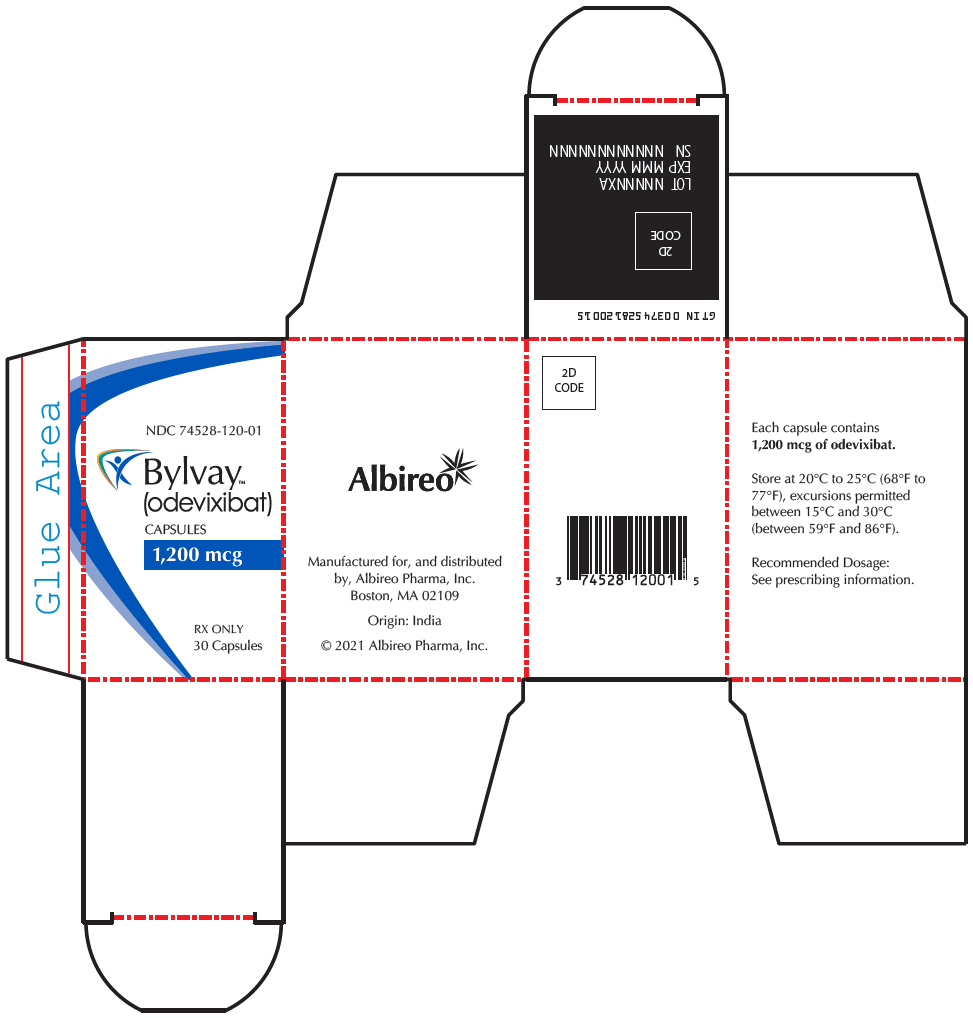 DRUG LABEL: BYLVAY
NDC: 74528-020 | Form: CAPSULE, COATED PELLETS
Manufacturer: Albireo Pharma, Inc.
Category: prescription | Type: HUMAN PRESCRIPTION DRUG LABEL
Date: 20251231

ACTIVE INGREDIENTS: odevixibat 200 ug/1 1
INACTIVE INGREDIENTS: Microcrystalline cellulose 39 mg/1 1; HYPROMELLOSE, UNSPECIFIED 0.8 mg/1 1

HIGHLIGHTS OF PRESCRIBING INFORMATION

These highlights do not include all the information needed to use BYLVAY safely and effectively. See full prescribing information for BYLVAY.
BYLVAY (odevixibat) capsules, for oral use
BYLVAY (odevixibat) oral pellets
Initial U.S. Approval: 2021

RECENT MAJOR CHANGES

Contraindications (4) | 03/2025
Warnings and Precautions (5.1) | 03/2025
Warnings and Precautions (5.3) | 12/2025

1 INDICATIONS AND USAGE

BYLVAY is an ileal bile acid transporter (IBAT) inhibitor indicated for:

Progressive Familial Intrahepatic Cholestasis (PFIC)

- the treatment of pruritus in patients 3 months of age and older with progressive familial intrahepatic cholestasis (PFIC). (1.1)

Limitation of Use:

BYLVAY is not recommended in a subgroup of PFIC type 2 patients with specific ABCB11 variants resulting in non-functional or complete absence of the bile salt export pump protein. (12.5, 14.1)

Alagille Syndrome (ALGS)

- the treatment of cholestatic pruritus in patients 12 months of age and older with Alagille syndrome (ALGS). (1.2)

2 DOSAGE AND ADMINISTRATION

Recommended Dosage

PFIC:

- Patients 3 months and older: 40 mcg/kg taken orally once daily. (2.1)
- If there is no improvement in pruritus after 3 months, the dosage may be increased in 40 mcg/kg increments up to 120 mcg/kg once daily, not to exceed a daily dosage of 6 mg/day. (2.1)

ALGS:

- Patients 12 months and older: 120 mcg/kg taken orally once daily. (2.2)

Preparation and Administration Instructions

- Administer BYLVAY in the morning with a meal. (2.4)
- Do not crush or chew capsules. (2.4)
- See full prescribing information for preparation and administration instructions. (2.4)

3 DOSAGE FORMS AND STRENGTHS

Oral Pellets: 200 mcg, 600 mcg (3)

Capsules: 400 mcg, 1200 mcg (3)

4 CONTRAINDICATIONS

Patients with prior or active hepatic decompensation events (e.g., variceal hemorrhage, ascites, hepatic encephalopathy). (4)

5 WARNINGS AND PRECAUTIONS

- Hepatoxicity: Obtain baseline liver tests and monitor patients frequently for the first 6 to 8 months after starting therapy, and as clinically indicated thereafter during treatment. If liver test abnormalities or signs of clinical hepatitis occur, consider dose reduction or treatment interruption. For persistent or recurrent liver test abnormalities relative to baseline, discontinue BYLVAY. Monitor patients with compensated cirrhosis or portal hypertension more frequently. Permanently discontinue BYLVAY if hepatic decompensation occurs. (2.3, 5.1)
- Diarrhea: Treat dehydration. Treatment interruption or discontinuation may be required for persistent diarrhea. (5.2)
- Fat-Soluble Vitamin (FSV) Deficiency: Obtain baseline levels and monitor during treatment. Supplement with FSV if deficiency is observed. If FSV deficiency persists or worsens despite FSV supplementation, consider discontinuing BYLVAY treatment.
  - Fracture: Consider interrupting BYLVAY treatment. Supplement with FSV if indicated.
  - Bleeding: Interrupt treatment with BYLVAY. Optimize treatment of FSV deficiency and consider restarting BYLVAY once the patient is clinically stable. (5.3)

6 ADVERSE REACTIONS

PFIC: Most common adverse reactions (>2%) are liver test abnormalities, diarrhea, abdominal pain, vomiting, and fat-soluble vitamin deficiency. (6.1)

ALGS: Most common adverse reactions (>5%) are diarrhea, abdominal pain, hematoma, and decreased weight. (6.1)

To report SUSPECTED ADVERSE REACTIONS, contact Albireo Pharma, Inc. at +1-855-252-4736, or FDA at 1-800-FDA-1088 or www.fda.gov/medwatch.

8 USE IN SPECIFIC POPULATIONS

Pregnancy: Based on animal data, may cause cardiac malformations (8.1)

FULL PRESCRIBING INFORMATION

1 INDICATIONS AND USAGE

1.1 Progressive Familial Intrahepatic Cholestasis (PFIC)

BYLVAY is indicated for the treatment of pruritus in patients 3 months of age and older with PFIC.

Limitations of Use

- BYLVAY is not recommended in a subgroup of PFIC type 2 patients with specific ABCB11 variants resulting in non-functional or complete absence of the bile salt export pump (BSEP) protein [see Clinical Pharmacology (12.5) and Clinical Studies (14.1)].

1.2 Alagille Syndrome (ALGS)

BYLVAY is indicated for the treatment of cholestatic pruritus in patients 12 months of age and older with ALGS.

2 DOSAGE AND ADMINISTRATION

2.1 Recommended Dosage for Progressive Familial Intrahepatic Cholestasis (PFIC) in Patients Aged 3 Months and Older

- The recommended dosage of BYLVAY is 40 mcg/kg taken orally once daily in the morning with a meal. Table 1 below shows the recommended once daily dosage by body weight.
- If there is no improvement in pruritus after 3 months, the dosage may be increased in 40 mcg/kg increments up to 120 mcg/kg once daily not to exceed a daily dosage of 6 mg/day.
- BYLVAY oral pellets are intended for use by patients weighing less than 19.5 kilograms.
- BYLVAY capsules are intended for use by patients weighing 19.5 kilograms or above.
  Table 1. Recommended Dosage for PFIC in Patients aged 3 months and older (40 mcg/kg/day)
  Body Weight (kg) | Once Daily Dosage (mcg)
  7.4 and below | 200
  7.5 to 12.4 | 400
  12.5 to 17.4 | 600
  17.5 to 25.4 | 800
  25.5 to 35.4 | 1,200
  35.5 to 45.4 | 1,600
  45.5 to 55.4 | 2,000
  55.5 and above | 2,400

2.2 Recommended Dosage for Alagille Syndrome (ALGS) in Patients Aged 12 Months and Older

- The recommended dosage of BYLVAY is 120 mcg/kg taken orally once daily in the morning with a meal. Table 2 below shows the recommended once daily dosage by body weight.
- BYLVAY oral pellets are intended for use by patients weighing less than 19.5 kilograms.
- BYLVAY capsules are intended for use by patients weighing 19.5 kilograms or above.

Table 2. Recommended Dosage for ALGS in Patients aged 12 months and older (120 mcg/kg/day)
Body Weight (kg) | Once Daily Dosage (mcg)
7.4 and below | 600
7.5 to 12.4 | 1,200
12.5 to 17.4 | 1,800
17.5 to 25.4 | 2,400
25.5 to 35.4 | 3,600
35.5 to 45.4 | 4,800
45.5 to 55.4 | 6,000
55.5 and above | 7,200

2.3 Dosage Modification for Management of Adverse Reactions

Tolerability for Alagille Syndrome (ALGS)

Dose reduction to 40 mcg/kg/day (Table 1) may be considered if tolerability issues occur in the absence of other causes. Once tolerability issues stabilize, increase to 120 mcg/kg/day.

Liver Test Abnormalities

Establish the baseline pattern of variability of liver tests prior to starting BYLVAY, so that potential signs of liver injury can be identified. Monitor liver tests (e.g., ALT [alanine aminotransferase], AST [aspartate aminotransferase], TB [total bilirubin], DB [direct bilirubin] and International Normalized Ratio [INR]) during treatment with BYLVAY. Interrupt BYLVAY if new onset liver test abnormalities occur or symptoms consistent with clinical hepatitis are observed [see Warnings and Precautions (5.1)].

Once the liver test abnormalities either return to baseline values or stabilize at a new baseline value, consider restarting BYLVAY at the recommended dosage [see Dosage and Administration (2.1, 2.2)]. Consider discontinuing BYLVAY permanently if liver test abnormalities recur.

Discontinue BYLVAY permanently if a patient experiences a hepatic decompensation event (e.g., variceal hemorrhage, ascites, hepatic encephalopathy).

2.4 Preparation and Administration Instructions

- For patients taking bile acid binding resins, take BYLVAY at least 4 hours before or 4 hours after taking a bile acid binding resin [see Drug Interactions (7.1)].
- Do not crush or chew capsules.
  Oral Pellets:
    - Mix the contents of the shell containing Oral Pellets into soft food or a liquid (as described below).
    - Discard the emptied shells. Do not let your child swallow the unopened shells containing the Oral Pellets.
      Administration Instructions for patients capable of swallowing soft food:
      1. Administer BYLVAY with the first morning meal.
      2. Place a small amount (up to 2 tablespoons [30 mL]) of soft food (apple sauce, oatmeal, banana or carrot puree, chocolate or rice pudding) in a bowl. Keep the soft food at, or cooler than, room temperature.
      3. Open the shell containing Oral Pellets and empty the contents into the bowl of soft food. Gently tap the Oral Pellet shell to ensure that all contents have been dispersed.
      4. If the dose requires more than one shell of Oral Pellets, repeat Step 3.
      5. Gently mix until well dispersed and administer the entire dose immediately.
      6. Follow the dose with breast milk, infant formula, or other age-appropriate liquid.
      7. Do not store the mixture for future use.
      8. For patients unable to swallow soft food, see the instructions below.
      Administration Instructions with liquids (Using an oral dosing syringe):
      1. Administer BYLVAY with the first morning meal.
      2. Open the shell containing Oral Pellets and empty the contents into a small mixing cup. Gently tap the shell containing Oral Pellets to ensure that all contents have been emptied into the mixing cup.
      3. If the dose requires more than one shell of Oral Pellets, repeat Step 2.
      4. Add 1 teaspoon (5 mL) of an age-appropriate liquid (for example, breast milk, infant formula, or water).
      5. Let the pellets sit in the liquid for approximately 5 minutes to allow complete wetting REMINDER: The Oral Pellets will not dissolve in the liquid.
      6. After 5 minutes, place the tip of the oral syringe completely into the mixing cup. Pull the plunger of the syringe up slowly to withdraw the liquid/pellet mixture into the syringe. Gently push the plunger down again to expel the liquid/pellet mixture back into the mixing cup. Do this 2 to 3 times to ensure complete mixing of the pellets into the liquid.
      7. Withdraw the entire contents into the oral syringe by pulling the plunger on the end of the syringe.
      8. Place the tip of the syringe into the front of the patient's mouth between the tongue and the side of the mouth, and then gently push the plunger down to squirt the liquid/pellet mixture between your child's tongue and the side of the mouth. Do not squirt liquid/pellet mixture in the back of the child's throat because this could cause gagging or choking.
      9. Do not administer via a bottle or "sippy cup" because the Oral Pellets will not pass through the opening. The oral pellets will not dissolve in liquid.
      10. Follow the dose with breast milk, infant formula, or other age-appropriate liquid.
      11. If any pellet/liquid mixture remains in the mixing cup, repeat Step 7 and Step 8 until the entire dose has been administered.
      12. Check the child's mouth to make sure all of the liquid/pellet mixture has been swallowed.
  Capsules:
    Administration Instructions:
      1. Take in the morning with a meal.
      2. Swallow the capsule whole with a glass of water.
      3. Alternatively, for patients unable to swallow the capsules whole, BYLVAY capsules may be opened, and sprinkled and mixed with a small amount of soft food, or mixed with an age-appropriate liquid. Follow directions above for oral pellets to prepare and administer such a mixture.

3 DOSAGE FORMS AND STRENGTHS

Oral Pellets:

- 200 mcg: capsule with ivory opaque cap and white opaque body; imprinted "A200" (black ink).
- 600 mcg: capsule with ivory opaque cap and body; imprinted "A600" (black ink).

Capsules:

- 400 mcg: capsule with medium orange opaque cap and white opaque body; imprinted "A400" (black ink).
- 1200 mcg: capsule with medium orange opaque cap and body; imprinted "A1200" (black ink).

4 CONTRAINDICATIONS

IBAT inhibitors, including BYLVAY, are contraindicated in patients with prior or active hepatic decompensation events (e.g., variceal hemorrhage, ascites, hepatic encephalopathy) [see Warnings and Precautions (5.1)].

5 WARNINGS AND PRECAUTIONS

5.1 Hepatoxicity

BYLVAY treatment is associated with a potential for drug-induced liver injury (DILI).

In the PFIC and ALGS trials, treatment-emergent elevations of liver tests or worsening of liver tests occurred. Of the six patients who experienced DILI, two underwent liver transplant.

Obtain baseline liver tests because some ALGS and PFIC patients have abnormal liver tests at baseline. Monitor patients frequently for the first 6 to 8 months after starting therapy and as clinically indicated thereafter during treatment with BYLVAY. Monitor for elevation in liver tests, for the development of liver-related adverse reactions, and for physical signs of hepatic decompensation. If liver test abnormalities or signs of clinical hepatitis occur in the absence of other causes, consider dose reduction or treatment interruption.

Permanently discontinue BYLVAY if a patient experiences the following:

- persistent or recurrent liver test abnormalities, or
- upon rechallenge, signs and symptoms consistent with clinical hepatitis, or
- a hepatic decompensation event.

The safety and effectiveness of BYLVAY have not been established in patients with decompensated cirrhosis. Monitor patients with compensated cirrhosis or portal hypertension more frequently and discontinue BYLVAY if hepatic decompensation occurs. IBAT inhibitors, including BYLVAY, are contraindicated in patients with prior or active hepatic decompensation events [see Contraindications (4)].

5.2 Diarrhea

In Trial 1, diarrhea in PFIC patients was reported in 2 (10%) placebo-treated patients, 9 (39%) BYLVAY-treated 40 mcg/kg/day patients and 4 (21%) BYLVAY-treated 120 mcg/kg/day patients. Treatment interruption due to diarrhea occurred in 2 patients with 3 events during treatment with BYLVAY 120 mcg/kg/day. Treatment interruption due to diarrhea ranged between 3 to 7 days [see Adverse Reactions (6.1)]. One patient treated with BYLVAY 120 mcg/kg/day withdrew from Trial 1 due to persistent diarrhea.

In Trial 3, diarrhea in ALGS patients was reported in 1 placebo-treated patient (6%) and in 10 (29%) BYLVAY-treated patients [see Adverse Reactions (6.1)]. No patients interrupted or permanently discontinued BYLVAY due to diarrhea.

If diarrhea occurs, monitor for dehydration and treat promptly. Interrupt BYLVAY dosing if a patient experiences persistent diarrhea. Restart BYLVAY at 40 mcg/kg/day when diarrhea resolves, and increase the dose as tolerated if appropriate. If diarrhea persists and no alternate etiology is identified, stop BYLVAY treatment.

5.3 Fat-Soluble Vitamin Deficiency

BYLVAY may adversely affect absorption of fat-soluble vitamins (FSV). FSV include vitamin A, D, E, and K (measured using INR levels). PFIC and ALGS patients can have FSV deficiency at baseline and are frequently supplemented with FSV.

In Trial 1 in PFIC patients, new onset or worsening of existing FSV deficiency was reported in 1 (5%) placebo-treated patient, and 3 (16%) BYLVAY-treated 120 mcg/kg/day patients; none of the patients treated with BYLVAY dosage 40 mcg/kg/day had new onset or worsening of existing FSV deficiency.

In Trial 3 in ALGS patients, new or worsening of existing FSV deficiency was reported in 3 (17.6%) placebo-treated patients and 3 (8.6%) BYLVAY-treated patients [see Adverse Reactions (6.1)].

Obtain serum FSV levels at baseline and monitor during treatment, along with any clinical manifestations of FSV deficiency. If FSV deficiency is diagnosed, supplement with FSV. If FSV deficiency persists or worsens despite adequate FSV supplementation, consider permanent discontinuation of BYLVAY depending on the benefit and risk balance.

If complications of FSV deficiency occur, consider interrupting BYLVAY treatment and reassess to ensure adequate supplementation with FSV. Consider restarting BYLVAY once the patient is clinically stable.

Bone Fracture

Fracture events have been observed with BYLVAY-treated patients in two open-label postmarketing studies (5% in PFIC patients and 4% in ALGS patients) [see Adverse Reactions (6)]. If fracture occurs, consider interrupting BYLVAY treatment and supplement with FSV if indicated.

Bleeding

Interrupt treatment with BYLVAY if bleeding occurs. Optimize treatment of FSV deficiency and consider restarting BYLVAY once the patient is clinically stable.

6 ADVERSE REACTIONS

The following adverse reactions are discussed in greater detail in other sections of the label:

- Hepatotoxicity [see Warnings and Precautions (5.1)]
- Diarrhea [see Warnings and Precautions (5.2)]
- Fat-Soluble Vitamin Deficiency [see Warnings and Precautions (5.3)]

6.1 Clinical Trials Experience

Because clinical trials are conducted under widely varying conditions, adverse reaction rates observed in the clinical trials of a drug cannot be directly compared to rates in the clinical trials of another drug and may not reflect the rates observed in practice.

PFIC Clinical Studies

Trial 1 is a randomized, double-blind, placebo-controlled, 24-week study of two dose levels of BYLVAY (40 mcg/kg and 120 mcg/kg) administered once daily [see Clinical Studies (14.1)]. Sixty-two patients were randomized (1:1:1) to receive one of the following:

- BYLVAY 40 mcg/kg/day (n=23),
- BYLVAY 120 mcg/kg/day (n=19), or
- Placebo (n=20).

Table 3 summarizes the frequency of adverse reactions reported in ≥2% and at a rate greater than placebo in patients treated with BYLVAY in Trial 1. The most common adverse reactions observed in Trial 1 included diarrhea, liver test abnormalities, vomiting, abdominal pain, and fat-soluble vitamin deficiency.

Table 3. Common Adverse Reactions [Adverse reactions that occurred in ≥2% of BYLVAY-treated patients] from a Clinical Study of BYLVAY in Patients with Progressive Familial Intrahepatic Cholestasis (Trial 1)
Adverse Reaction | Placebo N=20 n (%) | BYLVAY 40 mcg/kg/day N=23 n (%) | BYLVAY 120 mcg/kg/day N=19 n (%)
Diarrhea | 2 (10%) | 9 (39%) | 4 (21%)
Transaminases increased (ALT, AST) | 1 (5%) | 3 (13%) | 4 (21%)
Vomiting | 0 | 4 (17%) | 3 (16%)
Abdominal pain | 0 | 3 (13%) | 3 (16%)
Blood bilirubin increased | 2 (10%) | 3 (13%) | 2 (11%)
Fat-soluble vitamin deficiency (A, D, E) | 1 (5%) | 0 | 3 (16%)
Splenomegaly | 0 | 0 | 2 (11%)
Cholelithiasis | 0 | 0 | 1 (5%)
Dehydration | 0 | 0 | 1 (5%)
Fracture | 0 | 1 (4%) | 0

Trial 2 is an open-label, single-arm study in 116 patients with PFIC types 1, 2, 3, 4 and 6; four patients with benign recurrent intrahepatic cholestasis (BRIC) were also enrolled. BYLVAY 40 or 120 mcg/kg/day was administered once daily for 72 weeks, with the option to continue treatment beyond 72 weeks.

Adverse reactions were similar to those observed in Trial 1. However, fractures were reported in a total of 6 patients (5%) in Trial 2. Adverse reactions observed in Trial 2 in addition to those described in Table 3 included increased INR (16%), epistaxis (9%), constipation (8%), coagulopathy (3%), headache (3%), nausea (3%), rash (3%), iron deficiency anemia (3%), gastroesophageal reflux disease (2%), prolonged prothrombin time (2%); and variceal hemorrhage, stoma hemorrhage, hematochezia, and rectal hemorrhage (<1% each). Adverse reactions leading to treatment discontinuation were increased bilirubin levels, diarrhea, progression of disease, increased INR, irritability, and decreased weight.

There was a total of 19 (16%) patients who underwent surgical intervention in Trial 2, with one patient who had surgical biliary diversion (SBD) followed by liver transplant, 15 patients who underwent liver transplant alone, and three patients who underwent SBD alone. Overall, 11 of the 19 patients had these surgical interventions prior to Week 72.

ALGS Clinical Studies

Trial 3 is a randomized, double-blind, placebo-controlled, 24-week study of a single dose level of BYLVAY (120 mcg/kg) administered once daily [see Clinical Studies (14.2)]. Fifty-two patients were randomized (2:1) to receive one of the following:

- BYLVAY 120 mcg/kg/day (n=35), or
- Placebo (n=17).

Table 4 summarizes the frequency of adverse reactions in patients with ALGS, reported in ≥5% and at a rate greater than placebo in patients treated with BYLVAY in Trial 3. No patients discontinued study treatment due to an adverse reaction. The most common adverse reactions observed in Trial 3 included diarrhea, abdominal pain, hematoma, and decreased weight.

Table 4. Common Adverse Reactions [Adverse reactions that occurred in ≥5% of BYLVAY-treated patients] from a Clinical Study of BYLVAY in Patients with Alagille Syndrome (Trial 3)
Adverse Reaction | Placebo N=17 n (%) | BYLVAY 120 mcg/kg/day N=35 n (%)
Diarrhea | 1 (6%) | 10 (29%)
Abdominal Pain | 1 (6%) | 5 (14%)
Hematoma | 0 | 3 (9%)
Weight decreased | 0 | 2 (6%)

Trial 4 is an open-label, single-arm study in 50 pediatric patients with ALGS. BYLVAY 120 mcg/kg/day was administered once daily for 72 weeks, with the option to continue beyond 72 weeks. Adverse reactions observed in Trial 4 in addition to those described in Table 4 included FSV deficiency (vitamin D deficiency [14%], vitamin E deficiency [10%], vitamin K deficiency [6%]), ALT increased (6%), headache (6%), increased INR (6%), increased blood bilirubin (4%), increased AST (4%), coagulopathy (4%), fracture (4%); nausea, vomiting, hematemesis, hematochezia, epistaxis, and constipation (2% each). The most common reason for BYLVAY treatment discontinuation was increased bilirubin levels. One patient underwent liver transplant in Trial 4 prior to Week 72 with no patients underwent SBD.

Hepatotoxicity

BYLVAY treatment is associated with a potential for DILI.

In the PFIC and ALGS trials, treatment-emergent elevations of liver tests or worsening of liver tests occurred. Of the six patients who experienced DILI, two underwent liver transplant.

6.2 Postmarketing Experience

The following adverse reactions have been identified during post-approval use of BYLVAY. Because these reactions are reported voluntarily from a population of uncertain size, it is not always possible to reliably estimate their frequency or establish a causal relationship to drug exposure.

Gastrointestinal disorders: gastrointestinal hemorrhage, gingival hemorrhage, liver transplant
Investigations: gamma-glutamyltransferase increased, hemoglobin decreased
Nervous system disorders: extra-axial hemorrhage (subdural hemorrhage)
Respiratory, thoracic, and mediastinal disorders: epistaxis

7 DRUG INTERACTIONS

7.1 Bile Acid Binding Resins

Administer bile acid binding resins (e.g., cholestyramine, colesevelam, or colestipol) at least 4 hours before or 4 hours after administration of BYLVAY [see Dosage and Administration (2.3)]. Bile acid binding resins may bind odevixibat in the gut, which may reduce BYLVAY efficacy.

8 USE IN SPECIFIC POPULATIONS

8.1 Pregnancy

Risk Summary

Limited human data on the use of BYLVAY in pregnant women are insufficient to establish a drug-associated risk of major birth defects, miscarriage, or adverse developmental outcomes. Based on findings from animal reproduction studies, BYLVAY may cause cardiac malformations when a fetus is exposed during pregnancy. In pregnant rabbits treated orally with odevixibat during organogenesis, an increased incidence of malformations in fetal heart, great blood vessels, and other vascular sites occurred at all doses; maternal systemic exposure at the lowest dose was 2.1 times the maximum recommended dose (see Data). Odevixibat may inhibit the absorption of fat-soluble vitamins. FSV are essential for normal fetal growth and development. Monitor pregnant patients for FSV deficiency and supplement as needed. Increased supplementation of FSVs may be needed during pregnancy [see Warnings and Precautions (5.3) and Clinical Considerations]. Consider the woman's need for BYLVAY, the potential drug-related risks to the fetus, and the potential adverse outcomes from untreated maternal PFIC and ALGS.

The estimated background risk of major birth defects and miscarriage for the indicated population is unknown. In the U.S. general population, the estimated background risk of major birth defects and miscarriage in clinically recognized pregnancies is 2 to 4% and 15 to 20%, respectively.

There is a pregnancy safety study that monitors pregnancy outcomes in women exposed to BYLVAY during pregnancy. Pregnant women exposed to BYLVAY, or their healthcare providers, should report BYLVAY exposure by calling 1-855-252-4736.

Clinical Considerations

Fetal/Neonatal Adverse Reactions

Odevixibat may inhibit the absorption of fat-soluble vitamins (FSV). Monitor pregnant patients for FSV deficiency and supplement as needed. Increased supplementation of FSVs may be needed during pregnancy [see Warnings and Precautions (5.3)].

Data

Animal Data

In an embryo-fetal development study, pregnant rabbits received oral doses of 10, 30, or 100 mg/kg/day during the period of organogenesis. Fetuses from all maternal groups treated with odevixibat showed an increase in cardiovascular malformations, which included 5-chambered heart, small ventricle, large atrium, ventricular septum defect, misshapen aortic valve, dilated aortic arch, right sided and retroesophageal aortic arch, fusion of aortic arch and pulmonary trunk, ductus arteriosus atresia, and absence of subclavian artery. These malformations occurred at 2.1 times the maximum recommended dose and higher, based on AUC (area under the plasma concentration-time curve). Odevixibat was shown to cross the placenta in pregnant rats.

No adverse effects on embryo-fetal development were observed following oral administration of 100, 300, or 1,000 mg/kg/day in pregnant rats during organogenesis. An increase in skeletal variations (delayed/incomplete ossification and thick ribs) was observed at 1,000 mg/kg/day. Maternal systemic exposure to odevixibat at the maximum dose tested was 272 times the maximum recommended dose, based on AUC.

No adverse effects on postnatal development were observed in a pre- and postnatal development study, in which female rats were treated orally with up to 1,000 mg/kg/day during organogenesis through lactation. The maternal AUC for odevixibat at 1,000 mg/kg/day was 434 times the maximum recommended dose, based on AUC.

8.2 Lactation

Risk Summary

Odevixibat has low absorption following oral administration, and exposure of the infant to BYLVAY through breast milk is not expected at the recommended doses [see Clinical Pharmacology (12.3)]. There are no data on the presence of odevixibat in human milk, the effects on the breastfed infant, or the effects on milk production. BYLVAY may reduce absorption of fat-soluble vitamins [see Warning and Precautions (5.3)]. Monitor FSV levels and increase FSV intake, if FSV deficiency is observed during lactation. The developmental and health benefits of breastfeeding should be considered along with the mother's clinical need for BYLVAY and any potential adverse effects on the breastfed child from BYLVAY or from the underlying maternal condition.

8.4 Pediatric Use

The safety and effectiveness of BYLVAY have been established in pediatric patients 3 months to 17 years of age for the treatment of pruritus in PFIC. Use of BYLVAY in this age group is supported by evidence from one randomized, double-blind, placebo-controlled trial conducted in 62 patients with a confirmed diagnosis of PFIC type 1 or type 2 (Trial 1), and an open-label extension trial in PFIC patients (Trial 2) [see Adverse Reactions (6.1) and Clinical Studies (14.1)].

The safety and effectiveness of BYLVAY for the treatment of pruritus in PFIC in pediatric patients less than 3 months of age have not been established.

The safety and effectiveness of BYLVAY have been established in pediatric patients 12 months to 17 years of age for the treatment of pruritus in ALGS. Use of BYLVAY in this age group is supported by evidence from one randomized, double-blind, placebo-controlled trial conducted in 52 patients with a confirmed diagnosis of ALGS (Trial 3) and one open-label extension trial in ALGS patients (Trial 4) [see Adverse Reactions (6.1) and Clinical Studies (14.2)].

The safety and effectiveness of BYLVAY for the treatment of pruritus in ALGS in pediatric patients less than 12 months of age have not been established.

8.5 Geriatric Use

PFIC and ALGS are largely diseases of pediatric and young adult patients. Clinical studies in BYLVAY did not include patients 65 years of age and older.

8.6 Hepatic Impairment

Patients with PFIC and ALGS may have impaired hepatic function. The efficacy and safety of BYLVAY in PFIC and ALGS patients with clinically significant portal hypertension, and in patients with decompensated cirrhosis have not been established [see Dosage and Administration (2.3), Contraindications (4), Warning and Precautions (5.1), and Clinical Studies (14)].

11 DESCRIPTION

The active ingredient in BYLVAY (odevixibat) capsules and BYLVAY (odevixibat) oral pellets, an ileal bile acid transporter (IBAT) inhibitor, is (2S)-2-{[(2R)-2-(2-{[3,3-dibutyl-7-(methylsulfanyl)-1,1-dioxo-5-phenyl-2,3,4,5-tetrahydro-1H-1λ^6,2,5-benzothiadiazepin-8yl]oxy}acetamido)-2-(4-hydroxyphenyl)acetly]amino}butanoic acid, which is formulated as the sesquihydrate having the following chemical structure:

The molecular formula is C37H48N4O8S2 × 1.5 H2O, with a molecular weight of 768.0 g/mol (anhydrous 740.9 g/mol). Odevixibat sesquihydrate is a white to off-white solid. Its solubility in aqueous solutions is pH-dependent and increases with increased pH.

BYLVAY is available for oral administration as oral pellets containing odevixibat sesquihydrate equivalent to 200 mcg or 600 mcg of odevixibat, and as capsules containing odevixibat sesquihydrate equivalent to 400 mcg or 1200 mcg of odevixibat, and the following excipients: hypromellose and microcrystalline cellulose.

The capsule shells for the oral pellets contain hypromellose, titanium dioxide and yellow iron oxide.

The capsule shells for the capsules contain hypromellose, red iron oxide, titanium dioxide and yellow iron oxide.

The imprinting ink contains ferrosoferric oxide/black iron oxide and shellac glaze.

12 CLINICAL PHARMACOLOGY

12.1 Mechanism of Action

Odevixibat is a reversible inhibitor of the ileal bile acid transporter (IBAT). It decreases the reabsorption of bile acids (primarily the salt forms) from the terminal ileum.

Pruritus is a common symptom in patients with PFIC and ALGS; the pathophysiology of pruritus in patients with PFIC is not completely understood. Although the complete mechanism by which odevixibat improves pruritus in both PFIC and ALGS patients is unknown, it may involve inhibition of the IBAT, which results in decreased reuptake of bile salts, as observed by a decrease in serum bile acids [see Clinical Pharmacology (12.2)].

12.2 Pharmacodynamics

Odevixibat reduces serum bile acids in patients with PFIC and ALGS.

In Trial 1, a 24-week, randomized, double-blind, placebo-controlled trial conducted in 62 patients with a confirmed diagnosis of PFIC type 1 or type 2, the majority of patients (88.7%) had elevated serum bile acids above 100 mcmol/L at baseline [see Clinical Studies (14)]. Serum bile acids concentrations were reduced from baseline within 4-8 weeks of odevixibat treatment compared to placebo treatment. The decreased concentrations of serum bile acids fluctuated over time but generally were maintained during the treatment over 24 weeks. The extent of decrease in serum bile acids was similar between 40 and 120 mcg/kg.

Trial 3 is a 24-week, randomized, double-blind, placebo-controlled trial conducted in 52 patients with a confirmed diagnosis of ALGS who were administered treatment with BYLVAY 120 mcg/kg once daily [see Clinical Studies (14.2)]. At baseline, serum bile acids were variable ranging from 93 to 510 mcmol/L. Serum bile acid concentrations were reduced from baseline as early as Week 4 of odevixibat treatment and the reduction was generally maintained during treatment over 24 weeks.

12.3 Pharmacokinetics

In pediatric patients with PFIC, 6 months to 17 years of age who received BYLVAY 40 mcg/kg or 120 mcg/kg once daily with food in the morning, the measurable odevixibat concentrations ranged from 0.06 to 0.72 ng/mL, and odevixibat concentrations were below the limit of quantification (0.05 ng/mL) in the majority of plasma samples.

In pediatric patients with ALGS who received BYLVAY 120 mcg/kg once daily with food in the morning, the measurable odevixibat concentrations ranged from 0.05 to 3.4 ng/mL.

Following single and repeated oral administration of odevixibat from 0.1 to 3 mg in healthy adults, plasma concentrations of odevixibat were mostly below the limit of quantification (0.05 ng/mL); therefore, AUC and peak plasma concentration (Cmax) could not be calculated.

Following a single administration of odevixibat 7.2 mg in healthy adults, the mean (%CV) Cmax and AUC0-24h were 0.47 ng/mL (34.8) and 2.19 ng∙h/mL (36.2), respectively. No accumulation of odevixibat was observed following once-daily dosing.

Absorption

Odevixibat is minimally absorbed following oral administration. Following a single administration of odevixibat 7.2 mg in healthy adults, odevixibat Cmax is reached between 1 to 5 hours.

Sprinkle on Applesauce

When odevixibat 9.6 mg was administered after sprinkling the pellets on applesauce, decreases of 39% and 35% in Cmax and AUC0-24h, respectively, and delayed median Tmax from 3 hours to 4.5 hours were observed compared to administration of whole capsules (eight 1200 mcg capsules) under fasted conditions. The effect of sprinkling on soft food on systemic exposure is not clinically significant [see Dosage and Administration (2.3)].

Effect of Food

Concomitant administration of a high-fat meal (800-1000 calories with approximately 50% of total caloric content of the meal from fat) with a single dose of odevixibat 9.6 mg delayed median Tmax from 3 hours to 4.5 hours and resulted in decreases of 72% and 62% in Cmax and AUC0-24h, respectively, compared to administration under fasted conditions in healthy adults. The effect of food on the changes of systemic exposures to odevixibat is not clinically significant [see Dosage and Administration (2.3)].

Distribution

Human plasma protein binding of odevixibat is greater than 99% in vitro.

Elimination

Following a single oral dose of 7.2 mg odevixibat in healthy adults, the mean half-life (t1/2) was 2.36 hours.

Metabolism

In vitro, odevixibat was metabolized via mono-hydroxylation.

Excretion

Following a single radiolabeled odevixibat 3 mg oral dose in healthy adults, 82.9% of the dose was recovered in feces (97% unchanged) and less than 0.002% in the urine.

Drug Interaction Studies

Effect of Other Drugs on Odevixibat

Odevixibat is a substrate of P-glycoprotein (P-gp) but not a substrate of breast cancer resistance protein (BCRP).

Coadministration of itraconazole (a strong P-gp inhibitor) with a single dose of BYLVAY 7.2 mg increased odevixibat AUC0-24h by 66% and Cmax by 52%, which is not expected to have a clinically significant effect.

Effect of Odevixibat on Other Drugs

In in vitro studies, odevixibat was not an inhibitor of CYP isoforms 1A2, 2B6, 2C8, 2C9, 2C19, or 2D6 nor an inducer of CYP isoforms 1A2, 2B6, or 3A4.

Concomitant use of BYLVAY 7.2 mg once daily for 4 days with oral midazolam (a CYP3A4 substrate) in healthy adults decreased the AUC0-24h of midazolam and 1-OH midazolam by 29% and 13%, respectively, which is not expected to have a clinically relevant effect.

In in vitro studies, odevixibat did not inhibit the transporters P-gp; BCRP; organic anion transporter polypeptide 1B1 and 1B3(OATP1B1 and OATP1B3); organic anion transporter (OAT)1, OAT3; organic cation transporter 2 (OCT2), multidrug and toxin extrusion transporter 1 and 2K (MATE1 and MATE2K).

In a clinical drug interaction study with a lipophilic combination oral contraceptive containing ethinyl estradiol (EE) (0.03 mg) and levonorgestrel (LVN) (0.15 mg) conducted in healthy adult females, concomitant use of odevixibat had no impact on the AUC of LVN and decreased the AUC of EE by 17%, which is not expected to have a clinically relevant effect.

12.5 Pharmacogenomics

PFIC is a heterogenous disease caused by homozygous or compound heterozygous variants, with different PFIC subtypes occurring in the general population. PFIC1 is caused by variants in the ATP8B1 gene, which encodes FIC1. PFIC2 is caused by variants in the ABCB11 gene, which encodes BSEP. PFIC2 is further categorized into BSEP subgroups based on specific variants. The BSEP-1 subgroup includes patients with at least one p.D482G (c.1445A>G) or p.E297G (c.890A>G) variant, BSEP-2 includes patients with at least one missense variant other than p.D482G or p.E297G (non BSEP-1), and BSEP-3 includes patients with variants that are predicted to encode a non-functional protein. PFIC3 is caused by variants in the ABCB4 gene, which encodes MDR3. PFIC4 is caused by variants in the TJP2 gene, which encodes TJP2. PFIC6 is caused by variants in the MYO5B gene, which encodes MYO5B. Patients can be clinically diagnosed with PFIC without a known pathogenic variant.

PFIC2 is the most common subtype accounting for 37-90% of PFIC patients. The prevalence of BSEP-1, BSEP-2, and BSEP-3 subgroups are approximately 27%, 52%, and 21%, respectively, based on data from a global consortium characterizing the natural history of severe BSEP deficiency.

13 NONCLINICAL TOXICOLOGY

13.1 Carcinogenesis, Mutagenesis, Impairment of Fertility

Carcinogenesis

In 2-year carcinogenicity studies, odevixibat was not tumorigenic in rats or mice at oral doses up to 100 mg/kg/day. Systemic exposure to odevixibat (AUC) at the maximum dose studied in rats and mice was approximately 231 and 459 times the maximum recommended dose, respectively.

Mutagenesis

Odevixibat was negative in the in vitro bacterial reverse mutation (Ames) assay, the in vitro mouse lymphoma cell gene mutation assay, and the in vivo rat micronucleus test.

Impairment of Fertility

Odevixibat had no effects on fertility or reproductive function in male and female rats at oral doses of up to 1,000 mg/kg/day.

14 CLINICAL STUDIES

14.1 PFIC

The efficacy of BYLVAY was evaluated in Trial 1 (NCT03566238), a 24-week, randomized, double-blind, placebo-controlled trial. Trial 1 was conducted in 62 pediatric patients, aged 6 months to 17 years, with a confirmed molecular diagnosis of PFIC type 1 or type 2, and presence of pruritus at baseline. Patients with variants in the ABCB11 gene that predict non-function or complete absence of the bile salt export pump (BSEP) protein, who had experienced prior hepatic decompensation events, who had other concomitant liver disease, whose INR was greater than 1.4, whose ALT or total bilirubin was greater than 10-times the upper limit of normal (ULN), or who had received a liver transplant were excluded in Trial 1.

Patients were randomized to placebo (n=20), 40 mcg/kg (n=23), or 120 mcg/kg (n=19). Study drug was administered once daily with a meal in the morning. In patients weighing less than 19.5 kg or patients who could not swallow the whole capsule, study drug was sprinkled on soft food and then administered orally.

Median age (range) of the patients in Trial 1 was 3.2 (0.5 to 15.9) years; 3 patients were older than 12 years of age. Of the 62 patients, 50% were male and 84% were white; 27% had PFIC type 1, and 73% had PFIC type 2. The mean (standard error [SE]) scratching score in the 2 weeks prior to baseline was 2.9 (0.08). Baseline mean (SE) eGFR was 164 (30.6) mL/min/1.73 m^2. Baseline median (range) ALT, AST, and total bilirubin were 65 (16-798) U/L, 83.5 (32-405) U/L, and 2.2 (0.2-18.6) mg/dL, respectively.

In Trial 1, a total of 13 patients discontinued from trial prematurely either due to no improvement in pruritus (n=11) or due to adverse reactions (n=2); 5/20 (25%) patients discontinued from the placebo arm and 8/42 (19%) patients discontinued from the BYLVAY arms. A total of 11 of the 13 patients rolled over to Trial 2 to receive BYLVAY 120 mcg/kg/day. One patient treated with BYLVAY 120 mcg/kg/day withdrew from the trial due to an adverse reaction of diarrhea [see Adverse Reactions (6)].

Given the patients' young age, a single-item observer-reported outcome (ObsRO) was used to measure patients' scratching severity as observed by their caregiver twice daily (once in the morning and once in the evening). Scratching severity was assessed on a 5-point ordinal response scale, with scores ranging from 0 (no scratching) to 4 (worst possible scratching). Patients were included in Trial 1 if their average scratching score was greater than or equal to 2 (medium scratching) in the 2 weeks prior to baseline.

Table 5 presents the results of the comparison between BYLVAY and placebo on the mean of patients' percentage of ObsRO assessments over the 24-week treatment period that were scored as 0 (no scratching) or 1 (a little scratching). Patients treated with BYLVAY demonstrated greater improvement in pruritus compared with placebo. Figure 1 displays the mean of patients' worst weekly average scratching scores in each treatment group for each month, where the weekly average utilized the worst score from each day (morning or evening score).

Table 5: Efficacy Results Over the 24-Week Treatment Period in Patients with PFIC Type 1 or 2 in Trial 1
 | Placebo (n=20) | BYLVAY
 | Placebo (n=20) | 40 mcg/kg/day (n=23) | 120 mcg/kg/day (n=19)
Mean [Based on least squares means from analysis of covariance model with daytime and nighttime baseline pruritus scores as covariates and treatment group and stratification factors (i.e., PFIC type and age category) as fixed effects.] Percentage of Assessments Over the Treatment Period
Scored as 0 (No Scratching) or 1 (A Little Scratching) (%)
Mean (SE) | 13.2 (8.7) | 35.4 (8.1) | 30.1 (9.0)
Mean Difference vs Placebo (95% CI) |  | 22.2 (4.7, 39.6) | 16.9 (-2.0, 35.7)

Figure 1: Mean [Figure 1 presents least squares means Based on a mixed model repeated measure (MMRM) analysis accounting for baseline score, treatment group, time (in months), treatment-by-baseline interaction, treatment-by-time interaction, and stratification factors (i.e., PFIC type and age category). Missing data were accounted for using placebo-reference multiple imputation.] of the Worst Weekly Average Scratching Scores for Each Month in Trial 1

14.2 ALGS

The efficacy of BYLVAY was evaluated in Trial 3 (NCT04674761), a 24-week, randomized, double-blind, placebo-controlled trial. Trial 3 was conducted in 52 pediatric patients, aged 6 months to 15 years, with a confirmed diagnosis of ALGS and presence of pruritus at baseline. Patients who had decompensated liver disease, who had other concomitant liver disease, whose INR was greater than 1.4, whose ALT was greater than 10-times the upper limit of normal (ULN) at screening, whose total bilirubin was greater than 15-times the ULN at screening, or who had received a liver transplant were excluded from Trial 3.

Patients were randomized to placebo (n=17) or 120 mcg/kg (n=35). Study drug was administered once daily with a meal in the morning. In patients weighing less than 19.5 kg or patients who could not swallow the whole capsule, study drug was sprinkled on soft food and then administered orally.

Median age (range) of the patients in Trial 3 was 6.1 (1.7 to 15.5) years in the BYLVAY group and 4.2 (0.5 to 14.3) years in the placebo group; 5 patients were older than 12 years of age. Of the 52 patients, 52% were male and 83% were white; 92% of patients had the JAG1 mutation and 8% had the NOTCH2 mutation. The mean (standard deviation [SD]) scratching score in the 2 weeks prior to baseline was 2.9 (0.6). Baseline mean (SD) eGFR was 159 (51.4) mL/min/1.73 m^2. Baseline median (range) ALT, AST, and total bilirubin were 152 (39-403) U/L, 135 (57-427) U/L, and 2.0 (0.4-11.4) mg/dL, respectively.

Given the patients' young ages, a single-item observer-reported outcome (ObsRO) was used to measure patients' scratching severity as observed by their caregiver twice daily (once in the morning and once in the evening). Scratching severity was assessed on a 5-point ordinal response scale, with scores ranging from 0 (no scratching) to 4 (worst possible scratching). Patients were included in Trial 3 if the average scratching score was greater than or equal to 2 (medium scratching) in the 14 days prior to baseline.

Table 6 presents the results of the comparison between BYLVAY and placebo on the change from baseline in average scratching score based on ObsRO assessments to Month 6 (Weeks 21 to 24). The average scratching score for each patient for each month post-baseline was calculated by: (Step 1) averaging the morning scores and averaging the evening scores within a week; (Step 2) averaging the morning and evening weekly scores to yield a single weekly score; and finally (Step 3) averaging the 4 weekly scores within the month. The baseline average scratching score for each patient was calculated by averaging the weekly scores obtained in Step 2 across the 2 weeks prior to randomization and initiation of blinded treatment. Patients treated with BYLVAY demonstrated greater improvement in pruritus compared with placebo. Figure 2 displays the means (95% confidence interval) of patients' average scratching scores in each treatment group for each month.

Table 6: Efficacy Results in Patients with ALGS in Trial 3
 | Placebo (n=17) | BYLVAY 120 mcg/kg/day (n=35)
Baseline Average Scratching Score
Mean (SD) | 3.0 (0.6) | 2.8 (0.5)
Change from Baseline in Average Scratching Score to Month 6 (Weeks 21 to 24) [Based on least square means from a mixed-effect model for repeated measures (MMRM) for change from baseline to each month accounting for baseline average scratching score, baseline age stratification (<10, ≥10 years), baseline direct bilirubin, treatment group, time (in months), and treatment-by-time interaction.]
Mean (SE) | -0.8 (0.2) | -1.7 (0.2)
Mean Difference vs Placebo (95% CI) | -0.9 (-1.4, -0.3)
p-value | 0.002

Figure 2: Mean [Figure 2 presents means for baseline and least squares means for Month 1 to 6 Least squares means are based on a mixed model repeated measure (MMRM) analysis accounting for baseline average scratching score, baseline age stratification (<10, ≥10 years), baseline direct bilirubin, treatment group, time (in months), and treatment-by-time interaction.] of the Average Scratching Scores for Each Month in Trial 3

16 HOW SUPPLIED/STORAGE AND HANDLING

Oral Pellets

200 mcg Oral Pellets: supplied as Size 0 capsule with ivory opaque cap and white opaque body; imprinted "A200" (black ink). Supplied in bottles of 30 with child-resistant closure (NDC 74528-020-01).

600 mcg Oral Pellets: supplied as Size 0 capsule with ivory opaque cap and body; imprinted "A600" (black ink). Supplied in bottles of 30 with child-resistant closure (NDC 74528-060-01).

Capsules

400 mcg Capsule: supplied as Size 3 capsule with medium orange opaque cap and white opaque body; imprinted "A400" (black ink). Supplied in bottles of 30 with child-resistant closure (NDC 74528-040-01).

1,200 mcg Capsule: supplied as Size 3 capsule with medium orange opaque cap and body; imprinted "A1200" (black ink). Supplied in bottles of 30 with child-resistant closure (NDC 74528-120-01).

Storage and Handling:

Store at 20°C to 25°C (68°F to 77°F); excursions permitted between 15°C and 30°C (between 59°F and 86°F) [See USP Controlled Room Temperature].

17 PATIENT COUNSELING INFORMATION

Advise the patient to read the FDA-approved patient labeling (Instructions for Use).

Administration Instructions

Advise patients or their caregivers(s) to:

- Take BYLVAY in the morning with a meal. Do not swallow the 200 mcg or 600 mcg capsule(s) containing Oral Pellets whole. These are intended to be opened and the contents mixed into soft food or liquids [see Dosage and Administration (2.1, 2.2, 2.4)].
- Follow stepwise administration Instructions [see Dosage and Administration (2.4)] for Oral Pellets and Capsules for patients unable to swallow the capsules whole.
- Take BYLVAY at least 4 hours before or 4 hours after taking a bile acid binding resin (e.g., cholestyramine, colesevelam, or colestipol) [see Drug Interactions (7.1)].

Hepatotoxicity

Advise patients or their caregiver(s) that liver tests should be obtained before starting BYLVAY and periodically during BYLVAY therapy. Inform patients or their caregiver(s) of the potential risk of hepatotoxicity, and that they will need to undergo monitoring for liver injury. Instruct patients or their caregiver(s) to immediately report any signs or symptoms of severe liver injury to their healthcare provider [see Dosage and Administration (2.3) and Warnings and Precautions (5.1)].

Diarrhea

Advise patients or their caregiver(s) to notify their healthcare provider if they experience new onset or worsening of diarrhea [see Warnings and Precautions (5.2)].

Fat Soluble Vitamin (FSV) Deficiency

Advise patients or their caregiver(s) that INR (for vitamin K) and serum levels of vitamins A, D, E will be obtained before starting and periodically during treatment to assess for FSV deficiency [see Warnings and Precautions (5.3)]. Inform patients or their caregiver(s) that they may bleed more easily, may bleed longer, or have a bone fracture. Advise patients or their caregiver(s) to call their healthcare provider for any signs or symptoms of bleeding or report any fractures.

Pregnancy

Advise patients or their caregiver(s) that there is a pregnancy safety study that collects pregnancy outcome data in women taking BYLVAY during pregnancy. Pregnant women exposed to BYLVAY, or their healthcare providers, should report BYLVAY exposure by calling 1-855-252-4736 [see Use in Specific Populations (8.1)].

Manufactured for:

Albireo Pharma, Inc.
53 State Street
19th Floor
Boston, MA 02109

Instructions For Use BYLVAY [bil-vay] (odevixibat) Capsules, for oral use Oral Pellets

This Instructions for Use contains information on how to give BYLVAY Capsules and Oral Pellets. This information does not take the place of talking to your healthcare provider about your child's medical condition or their treatment.

Important information you need to know before giving or taking BYLVAY

- Give BYLVAY along with the morning meal.
- Mix BYLVAY in a small amount of soft food (up to 2 tablespoons [30 mL]), such as apple sauce, oatmeal, banana or carrot puree, chocolate or rice pudding, in a bowl. You may also mix BYLVAY with an age-appropriate liquid and give through an oral syringe.
- If your child is taking bile acid binding resins (for example, cholestyramine, colestipol), give them BYLVAY at least 4 hours before or 4 hours after they take the bile acid binding resin.

Preparing to Give BYLVAY

You will be provided with the number of BYLVAY Capsules or Oral Pellets prescribed by your child's healthcare provider in a child-resistant closure.

Giving BYLVAY Oral Pellets with soft food:

- The shell containing Oral Pellets are to be opened and sprinkled. Do not let your child swallow the shell containing the Oral Pellets. Dispose of (throw away) the emptied shell.
- Mix the contents of the Oral Pellets with soft food as shown in Steps 1 through 9 below.
  Step 1. | Give BYLVAY with the first morning meal. Place a small amount of soft food (up to 2 tablespoons [30 mL], such as apple sauce, oatmeal, banana or carrot puree, chocolate or rice pudding) in a bowl. Keep the soft food at, or cooler than, room temperature. Note: This small amount of soft food should be less than what your child would normally eat.
  Step 2. | Hold the shell containing Oral Pellets horizontally on both ends, twist in opposite directions and pull apart (see Figure A).
   | Figure A
  Step 3. | Empty the Oral Pellets into the bowl of soft food (see Figure B).
   | Figure B
  Step 4. | Gently tap the shell containing Oral Pellets to make sure that all pellets come out (see Figure C).
   | Figure C
  Step 5. | If the dose requires more than 1 capsule shell, repeat Step 2 and Step 3.
  Step 6. | Gently mix the Oral Pellets with a spoon into the soft food. Note that the Oral Pellets will not dissolve (see Figure D).
   | Figure D
  Step 7. | Give the entire dose right away after mixing. Do not store the BYLVAY mixture for later use.
  Step 8. | Give water or an age-appropriate liquid, such as breast milk or infant formula, after the dose is taken.
  Step 9. | Dispose of (throw away) the empty Oral Pellet shells in the trash.

Giving BYLVAY Oral Pellets with liquids (Using an oral dosing syringe):

- The shell containing the Oral Pellets are to be opened.
- Mix the Oral Pellets with liquid as shown in Steps 1 through 14 below.
- Dispose of (throw away) the emptied shells. Do not let your child swallow the unopened shells containing the Oral Pellets.
  Step 1. | Give BYLVAY with the first morning meal.
  Step 2. | Hold the shell containing the Oral Pellets horizontally on both ends, twist in opposite directions and pull apart (see Figure A).
  Step 3. | Empty the Oral Pellets into a small mixing cup. Gently tap the Oral Pellet shell to ensure that all contents have been emptied into the mixing cup (see Figure E).
  Figure E
  Step 4. | If the dose requires more than 1 capsule shell, repeat Step 2 and Step 3.
  Step 5. | Add 1 teaspoon (5 mL) of an age-appropriate liquid (for example, breast milk, infant formula, or water).
  Step 6. | Let the pellets sit in the liquid for about 5 minutes to allow complete wetting. REMINDER: The pellets will not dissolve in the liquid.
  Step 7. | After 5 minutes, place the tip of the oral syringe completely into the mixing cup. Pull the plunger of the syringe up slowly to withdraw the liquid and pellet mixture into the syringe. Gently push the plunger down again to expel the liquid and pellet mixture back into the mixing cup. Do this 2 to 3 times to ensure complete mixing of the pellets into the liquid.
  Step 8. | Withdraw the entire contents into the syringe by pulling the plunger on the end of the syringe (see Figure F).
  Figure F
  Step 9. | Place the tip of the syringe into the front of the child's mouth between the tongue and the side of the mouth, and then gently push the plunger down to squirt the liquid and pellet mixture between the tongue and the side of the mouth. Do not squirt the liquid and pellet mixture in the back of the throat because this could cause gagging or choking (see Figure G).
  Figure G
  Step 10. | Do not give using a bottle or "sippy cup" because the Oral Pellets will not pass through the opening. The oral pellets will not dissolve in liquid.
  Step 11. | Give water or an age-appropriate liquid such as breast milk or infant formula after the dose is taken.
  Step 12. | Repeat Steps 8 and 9 until the entire dose has been given.
  Step 13. | Check to make sure all of the liquid and pellet mixture has been swallowed.
  Step 14. | Dispose of (throw away) the empty Oral Pellet shells in the trash.

Taking BYLVAY Capsules

- Take BYLVAY Capsules along with your morning meal. Swallow BYLVAY Capsules whole with a glass of water. Do not chew or crush the Capsules.
- For children unable to swallow BYLVAY Capsules whole, follow instructions under Preparing to Give BYLVAY above.

How should I store BYLVAY Capsules or Oral Pellets?

Store BYLVAY at room temperature between 68°F to 77°F (20°C to 25°C).

Disposing (throwing away) of BYLVAY Capsules or Oral Pellets shells.

Dispose of (throw away) the empty BYLVAY Capsule or Oral Pellets shells in the household trash.

What are the ingredients in BYLVAY?

Active ingredient: odevixibat.

Inactive ingredients: hypromellose and microcrystalline cellulose.

Manufactured for:

Albireo Pharma, Inc.
53 State Street
19th Floor
Boston, MA 02109

This Instructions for Use has been approved by the U.S. Food and Drug Administration.
Approved: 10/2022

PRINCIPAL DISPLAY PANEL - 200 mcg Capsule Bottle Carton

NDC 74528-020-01

Bylvay™
(odevixibat)

ORAL PELLETS

200 mcg

RX ONLY
30 Capsules

PRINCIPAL DISPLAY PANEL - 400 mcg Capsule Bottle Carton

NDC 74528-040-01

Bylvay™
(odevixibat)

CAPSULES

400 mcg

RX ONLY
30 Capsules

PRINCIPAL DISPLAY PANEL - 600 mcg Capsule Bottle Carton

NDC 74528-060-01

Bylvay™
(odevixibat)

ORAL PELLETS

600 mcg

RX ONLY
30 Capsules

PRINCIPAL DISPLAY PANEL - 1,200 mcg Capsule Bottle Carton

NDC 74528-120-01

Bylvay™
(odevixibat)

CAPSULES

1,200 mcg

RX ONLY
30 Capsules